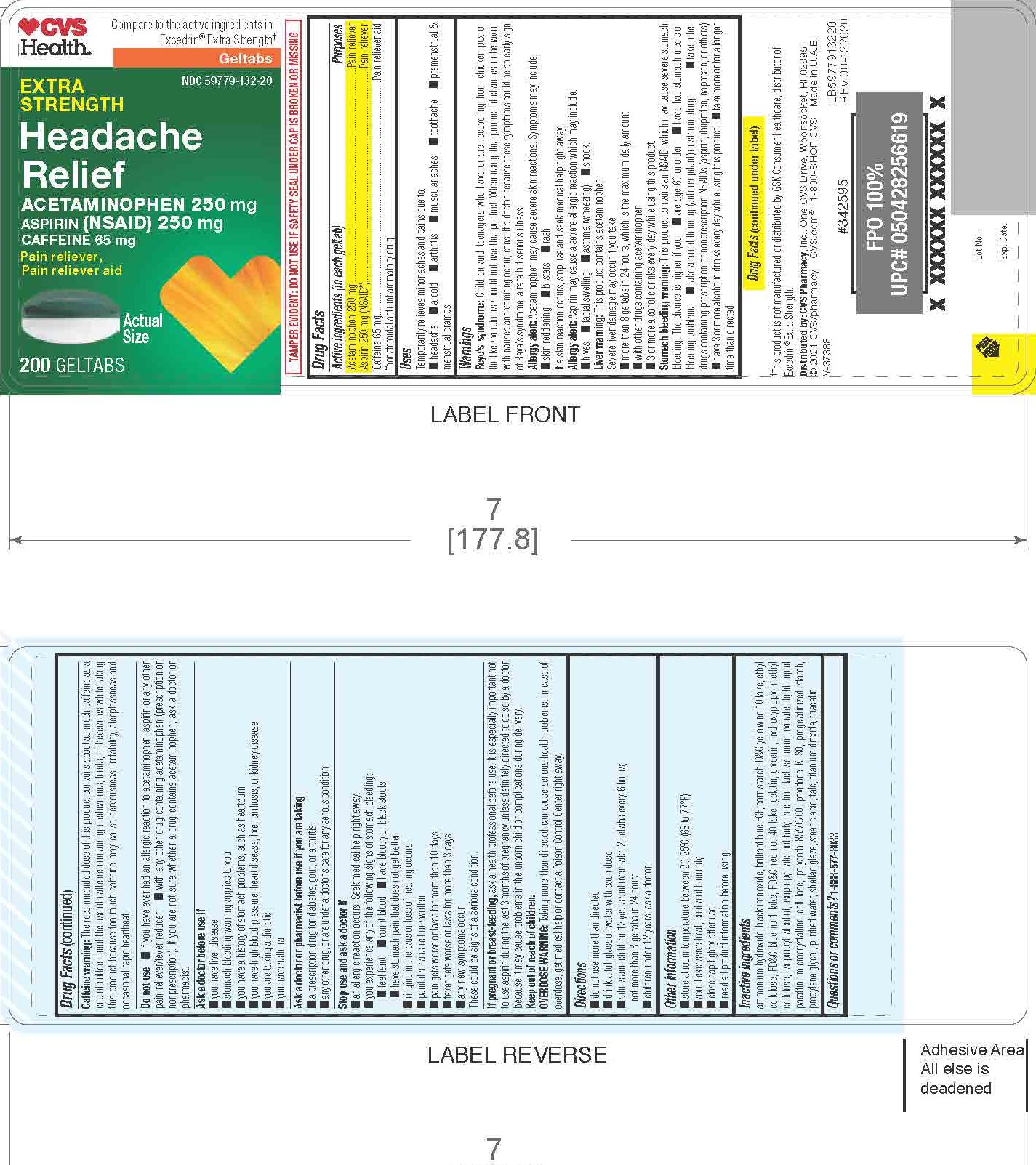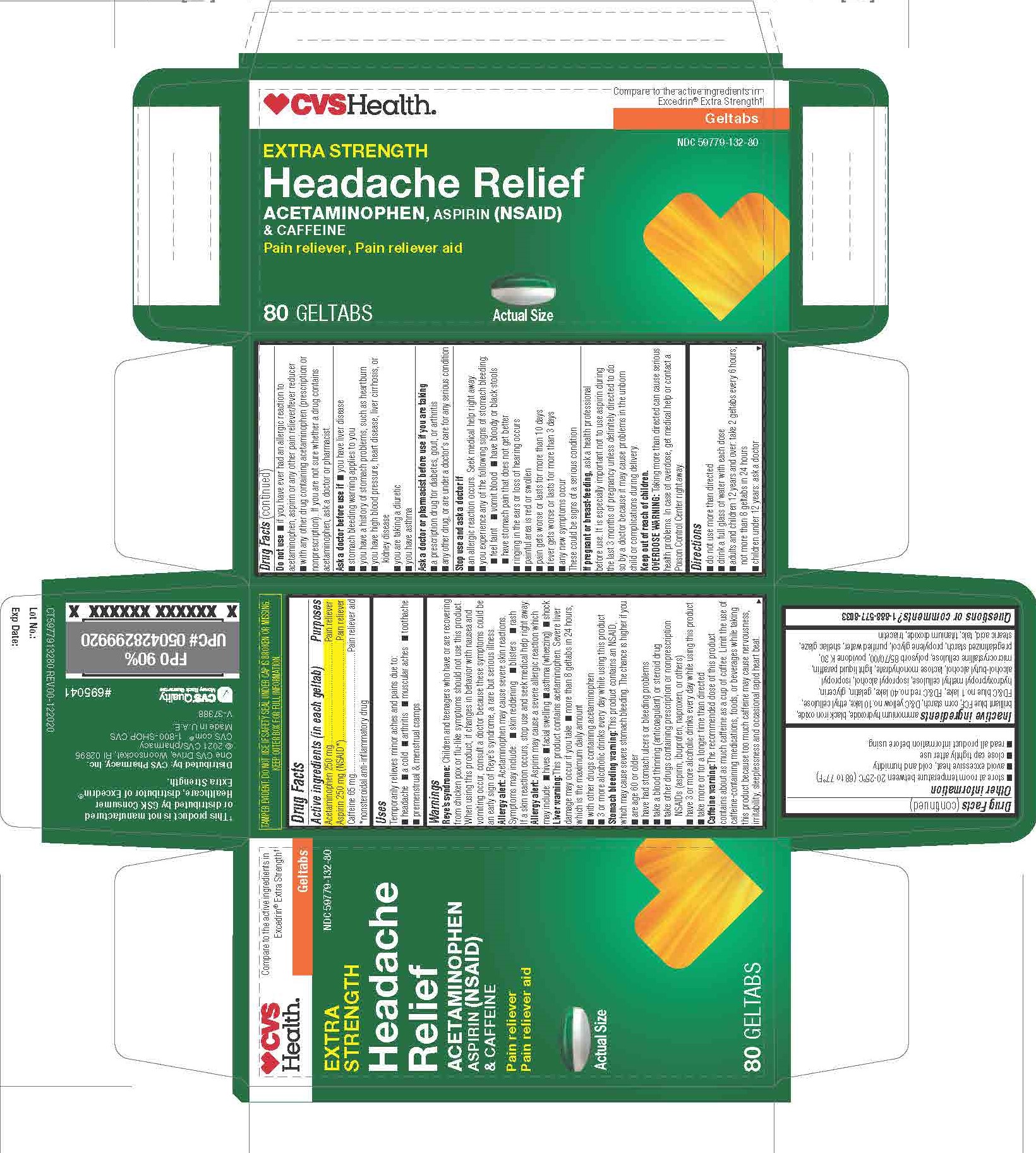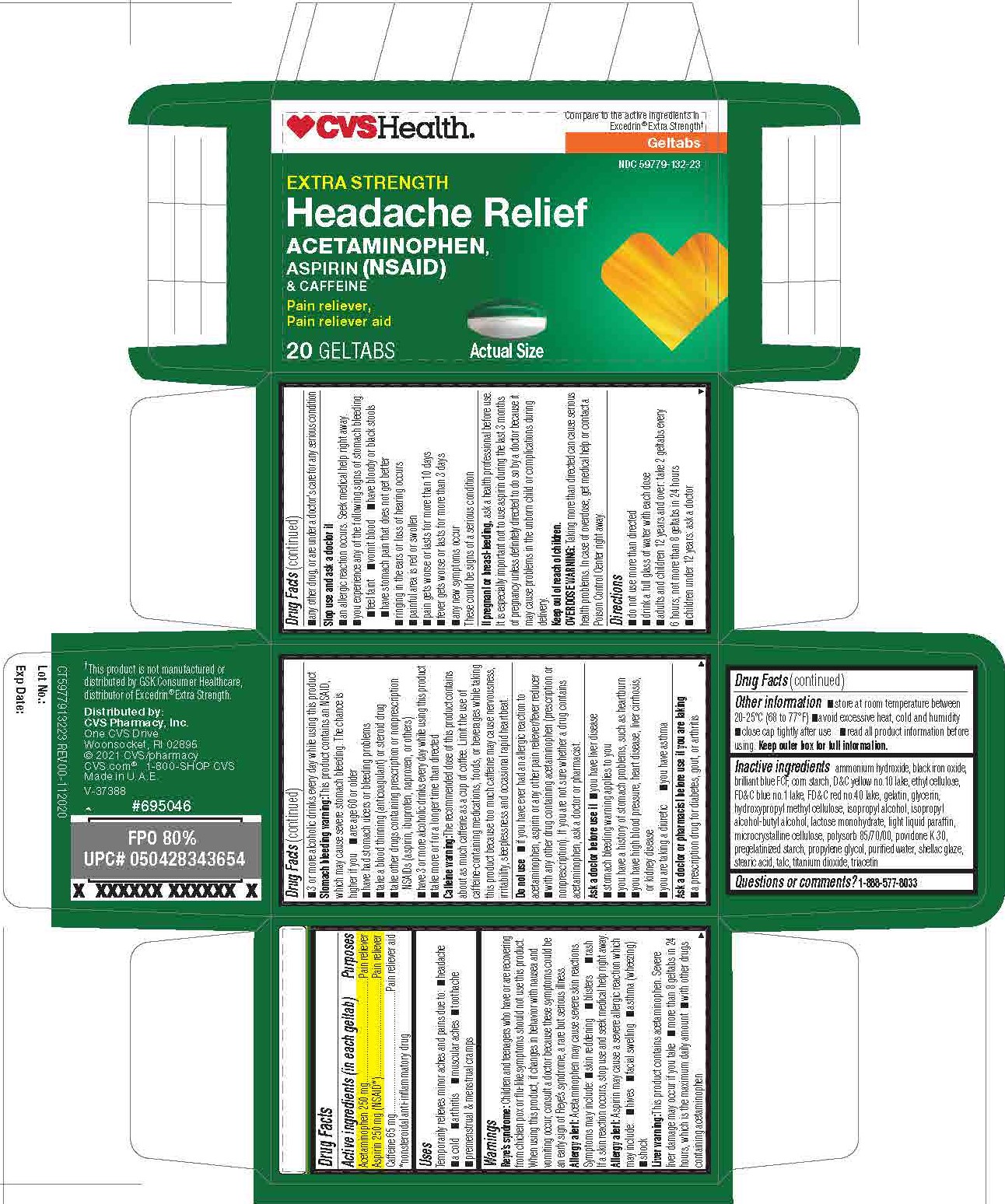 DRUG LABEL: Acetaminophen 250mg Aspirin 250mg Caffeine 65mg
NDC: 69842-591 | Form: TABLET
Manufacturer: CVS Pharmacy
Category: otc | Type: HUMAN OTC DRUG LABEL
Date: 20241214

ACTIVE INGREDIENTS: ACETAMINOPHEN 250 mg/1 1; ASPIRIN 250 mg/1 1; CAFFEINE 65 mg/1 1
INACTIVE INGREDIENTS: FD&C RED NO. 40; GELATIN, UNSPECIFIED; D&C YELLOW NO. 10; PROPYLENE GLYCOL; STEARIC ACID; TITANIUM DIOXIDE; LIGHT MINERAL OIL; ETHYLCELLULOSE, UNSPECIFIED; GLYCERIN; LACTOSE MONOHYDRATE; POVIDONE, UNSPECIFIED; FERROSOFERRIC OXIDE; FD&C BLUE NO. 1; STARCH, CORN; AMMONIA; MICROCRYSTALLINE CELLULOSE; SORBITOL SOLUTION; TALC; SHELLAC; TRIACETIN; HYPROMELLOSE, UNSPECIFIED

CVS Headache Relief Geltabs
Acetaminophen 250mg, Aspirin 250mg, Caffeine 65mg

ACTIVE INGREDIENT

Acetaminophen 250mg

Aspirin 250mg

Caffeine 65mg

INACTIVE INGREDIENT

ammonium hydroxide, black iron oxide, brilliant blue FCF, corn starch, D&C yellow No. 10 lake, ethyl cellulose, FD&C blue No. 1 lake, FD&C red No. 40 lake, gelatin, glycerin, hydroxypropyl methyl cellulose, lactose monohydrate, light liquid paraffin, microcrystalline cellulose, povidone, pregelatinised starch, propylene glycol, shellac glaze, sorbitol sorbitan, stearic acid, talc, titanium dioxide, triacetin.

- Do not use more than directed
- Drink a full glass of water with each dose
- Adults and children 12 years and over: take 2 geltabs every 6 hours; not more than 8 geltabs in 24 hours
- Children under 12 years: ask a doctor

INDICATIONS AND USAGE

Temporarily relieves minor aches and pains due to:

Headache, a cold, arthritis, muscular aches, toothache, premenstrual and menstrual cramps

WARNINGS

Reye’s syndrome: Children and teenagers who have or are recovering from chicken pox or flu-like symptoms should not use this product. When using this product, if changes in behavior with nausea and vomiting occur, consult a doctor because these symptoms could be an early sign of Reye’s syndrome, a rare but serious illness.

Allergy alert: Acetaminophen may cause severe skin reactions. Symptoms may include: skin reddening, blisters, rash. If a skin reaction occurs, stop use and seek medical help right away.

Allergy alert: Aspirin may cause a severe allergic reaction which may include: hives, facial swelling, asthma (wheezing), shock.

Liver warning: This product contains acetaminophen. Severe liver damage may occur if you take more than 8 geltabs in 24 hours, which is the maximum daily amount, with other drugs contains acetaminophen, 3 or more alcoholic drinks every day while using this product.

Stomach bleeding warning: This contains an NSAID, which mat cause severe stomach bleeding. The chance is higher if you are age 60 or older, have had stomach ulcers or bleeding problems, take a blood thinning (anticoagulant) or steroid drug, take other drugs containing prescription or nonprescription NSAIDs (aspirin, ibuprofen, naproxen, or others), have 3 or more alcoholic drinks every day while using product, take more or for a longer time than direct.

Caffeine warning: The recommended dose of this product contains about as much caffeine as a cup of coffee. Limit the use of caffeine-containing medications, foods, or beverages while taking this product because too much caffeine may cause nervousness, irritability, sleeplessness, and, occasionally, rapid heartbeat.

Do not use if you have ever had an allergic reaction to acetaminophen, aspirin, or any other pain reliever/ fever, with any other drug containing acetaminophen (prescription or nonprescription). If you are not sure whether a drug contains acetaminophen, ask a doctor or pharmacist.

Ask a doctor before use if you have liver disease, stomach bleeding warning applies to you, you have a history of stomach problems, such as heartburn, you have high blood pressure, heart disease, liver cirrhosis, or kidney disease, you are taking a diuretic, you have asthma.

Ask a doctor or pharmacist before use if you are taking a prescription drug for diabetes, gout, or arthritis, any other drug, or are under a doctor’s care for any serious condition.

Stop use and ask a doctor if an allergic reaction occurs. Seek medical help right away. You experience any of the following signs of stomach bleeding: feel faint, vomit blood, have bloody or black stools, have stomach pain that does not get better, ringing in the ears or loss of hearing occurs, painful area is red or swollen, pain gets worse or lasts for more than 10 days, fever gets worse or lasts for more than 3 days, any new symptoms occur. These could be signs of a serious condition.

If pregnant or breast-feeding, ask a health professional before use. It is especially important not to use aspirin during the last 3 months of pregnancy unless definitely to do so by a doctor because it may cause problems in the unborn child or complications during delivery.

Keep out of reach of children.

Keep out of reach of children.

OVERDOSE WARNING: Taking more than directed can cause serious health problems. In case of overdose, get medical help or contact a Poison Control Center right away.

PURPOSE

Pain reliever

Pain reliever

Pain reliever aid

OTHER SAFETY INFORMATION

- Store at room temperature between 20-25 ºC (68-77 ºF)
- Avoid excessive heat, cold, and humidity
- Close cap tightly after use
- Read all product information before using. Keep box for important information.